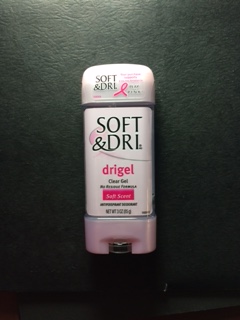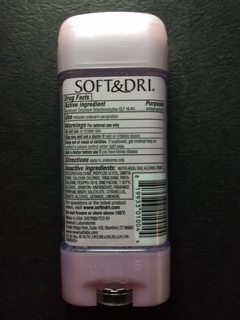 DRUG LABEL: Soft and Dri drigel
NDC: 69752-102 | Form: STICK
Manufacturer: The Village Company
Category: otc | Type: HUMAN OTC DRUG LABEL
Date: 20191220

ACTIVE INGREDIENTS: ALUMINUM ZIRCONIUM OCTACHLOROHYDREX GLY 164 mg/1 g
INACTIVE INGREDIENTS: DIMETHICONE

Active Ingredient

Aluminum Zirconium Octachlorohydrex Gly (16.4%)

PURPOSE

Antiperspirant

Use

reduces underarm perspiration

Warnings For external use only

Stop use and ask a doctor if

rash or irritation occurs

Keep out of reach of chlidren

If swallowed, get medical help or contact a posion control center right away

Ask a doctor before use if

you have kidney disease

Do not use

on broken skin

Directions

Apply to underarms only.

DOSAGE AND ADMINISTRATION

Apply to underarms only.

Inactive ingredients

Water, (Auqua, EAU), Alcohol denat., Cyclopentsiloxane, Propylene Glycol, Dimethicone, Calcium cholride, Trisiloxane, Pentasiloxane, PEG/PPG-18/18, Dimethicone, T-butyl alcohol, Denaton-ium Benzoate, Fragrance (Parfum), Benzyl Salicylate, Cirtronellol, Benzyl Alcohol, Geraniol, Limonene